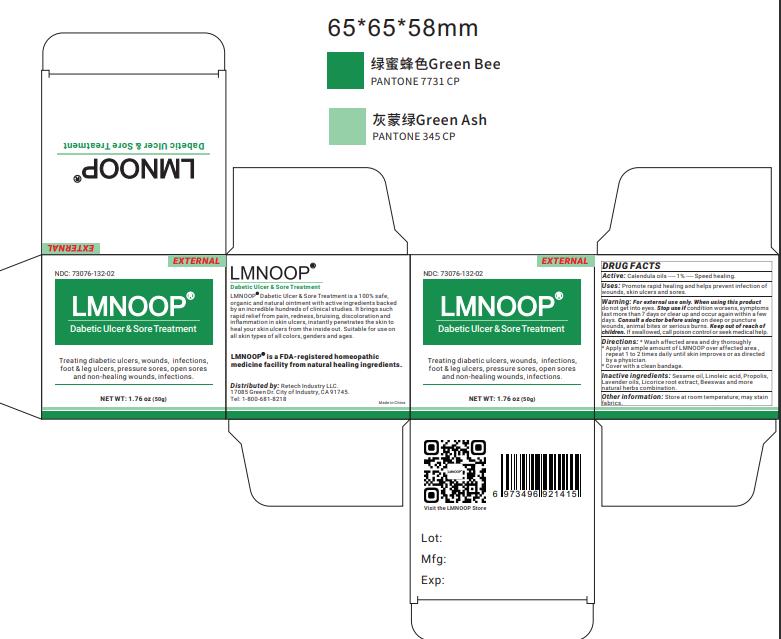 DRUG LABEL: skin ulcer
NDC: 73252-135 | Form: OINTMENT
Manufacturer: Hunan Xiong Shi Pharmaceutical Co., Ltd
Category: homeopathic | Type: HUMAN OTC DRUG LABEL
Date: 20241019

ACTIVE INGREDIENTS: CALENDULA OFFICINALIS FLOWER 1 g/100 g
INACTIVE INGREDIENTS: CORYMBIA CITRIODORA LEAF OIL; GANODERMA LUCIDUM WHOLE 5 g/100 g; ANGELICA SINENSIS ROOT 2 g/100 g; GLYCYRRHIZA URALENSIS 3 g/100 g; SOPHORA FLAVESCENS ROOT 3 g/100 g; SESAME OIL 52 g/100 g; PROPOLIS WAX 5 g/100 g; YELLOW WAX 20 g/100 g; LINOLEIC ACID 5 g/100 g

Active ingreddient

Calendula oils ---1%----Speed healing.

Inactive ingredients:

Bees Wax, Linoleic Acid, Propolis, Sesame oil, Glycyrrhiza glabra, Panax notoginseng root, Cullen corylifolium seed, Calamus draco willd, Geranium oils.

Ask doctor if

on deep or puncture wounds, animal bites or serious burns.

do not

get into eyes

USES

Promote rapid healing and helps prevent infection of wounds, skin ulcers and sores.

Stop use if

condition worsens, symptoms last more than 7 days or clear up and occur again within a few days.

Warning

For external use only

Other information:

Store at room temperature; may stain fabrics.

Keep out of reach of children

if swallowed, call poison control or seek medical help.

Directions

Wash and dry affected area, apply a thin layer of LMNOOP over affected area, gently massage until fully absorbed, repeat 2-3 times daily.

Lable

Dabetic Ulcer & Sore Treatment